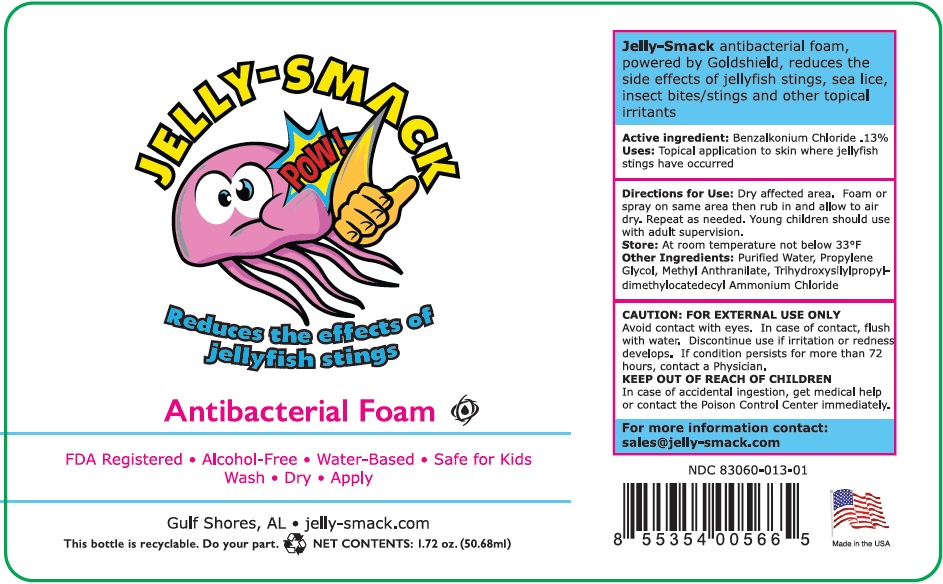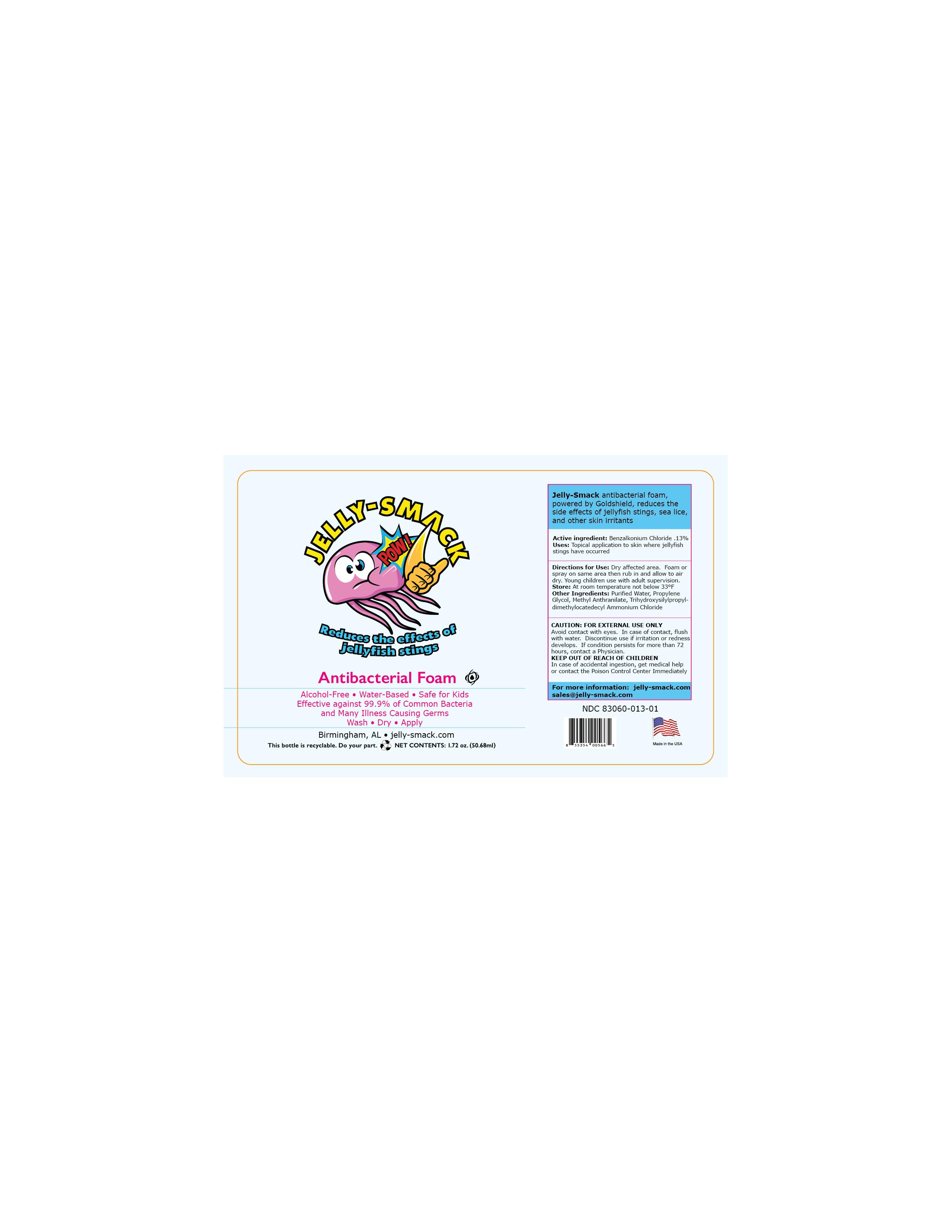 DRUG LABEL: Jelly Smack
NDC: 83060-013 | Form: SOLUTION
Manufacturer: VULCAN MICROBIAL CORPORATION
Category: otc | Type: HUMAN OTC DRUG LABEL
Date: 20250930

ACTIVE INGREDIENTS: BENZALKONIUM CHLORIDE 0.13 g/1 mL
INACTIVE INGREDIENTS: WATER 1 mL/1 mL

PURPOSE

Jelly-Smack antibacterial foam, powered by Goldshield, reduces the side effects of jellyfish stings, sea lice, and other skin irritants.

Active Ingredient

Benzalkonium Chloride .013%

Uses

Topical application to skin where jellyfish stings have occurred.

Store

At room temperature not below 33°F

Directions for Use

Dry affected area. Foam or spray on same area then rub in and allow to air dry. Young children use with adult supervision.

Other Ingredients

Purified Water, Propylene Glycol, Methyl Anthranilate, Trihydroxysilylpropyl-dimenthylocatedecyl Ammonium Chloride

CAUTION: FOR EXTERNAL USE ONLY

Avoid contact with eyes. In case of contact, flush with water. Discontinue use if irritation or redness develops. If condition persists for more than 72 hours, contact a Physician.

KEEP OUT OF REACH OF CHILDREN

In case of accidental ingestion, get medical help or contact the Poison Control Center Immediately

For more information:

jelly-smack.com sales @jelly-smack.com